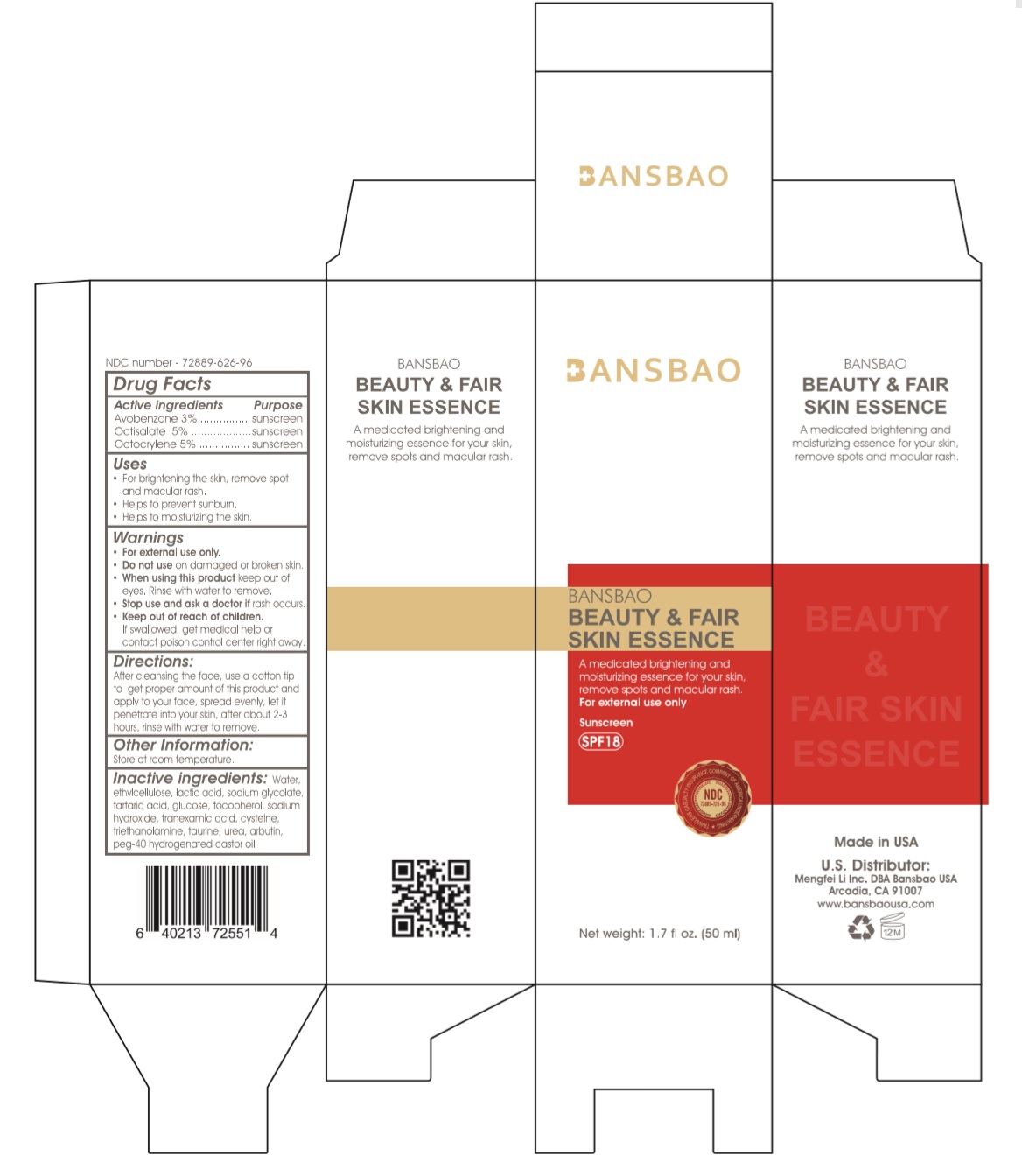 DRUG LABEL: BANSBAO BEAUTY AND FAIR SKIN ESSENCE
NDC: 72889-626 | Form: CREAM
Manufacturer: Mengfei Li  Inc.
Category: otc | Type: HUMAN OTC DRUG LABEL
Date: 20190327

ACTIVE INGREDIENTS: AVOBENZONE 3 g/100 mL; OCTISALATE 5 g/100 mL; OCTOCRYLENE 5 g/100 mL
INACTIVE INGREDIENTS: WATER; ETHYLCELLULOSE, UNSPECIFIED; LACTIC ACID, UNSPECIFIED FORM; SODIUM GLYCOLATE; TARTARIC ACID; ANHYDROUS DEXTROSE; TOCOPHEROL; SODIUM HYDROXIDE; TRANEXAMIC ACID; CYSTEINE; TROLAMINE; TAURINE; UREA; ARBUTIN; POLYOXYL 40 HYDROGENATED CASTOR OIL

BANSBAO BEAUTY & FAIR SKIN ESSENCE

Active ingredients

Avobenzone 3%

Octisalate 5%

Octocrylene 5%

Purpose

Sunscreen

Uses

- For brightening the skin, remove spot and macular rash.
- Helps to prevent sunburn.
- Helps to moisturizing the skin.

Warnings

- For external use only.
- Do not use on damaged or broken skin.
- When using this product keep out of eyes. Rinse with water to remove.
- Stop use and ask a doctor if rash occurs.

Keep out of reach of children. If swallowed, get medical help or contact poison control center right away.

Directions:

After cleansing the face, use a cotton tip to get proper amount of this product and apply to your face, spread evenly, let it penetrate into your skin, after about 2-3 hours, rinse with water to remove.

Other Information:

Store at room temperature.

Inactive ingredients:

Water, ethylcellulose, lactic acid, sodium glycolate, tartaric acid, glucose, tocopherol, sodium hydroxide, tranexamic acid, cysteine, triethanolamine, taurine, urea, arbutin, peg-40 hydrogenated castor oil.

A medicated brightening and moisturizing essence for your skin, remove spots and macular rash.

Sunscreen

SPF18

Made in USA

U.S. Distributor:

Mengfei Li Inc. DBA Bansbao USA

Arcadia, CA 91007

www.bansbaousa.com